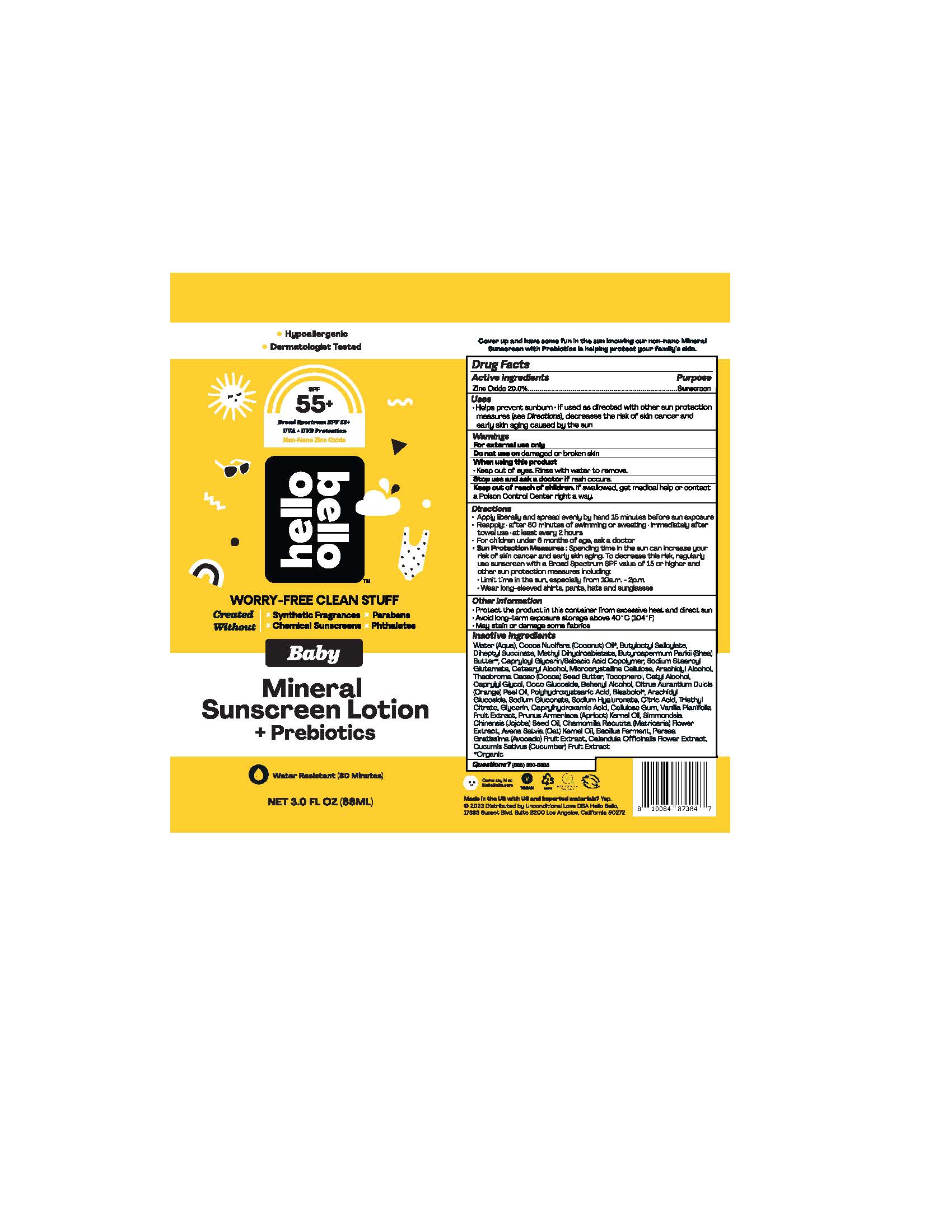 DRUG LABEL: Baby Mineral Sunscreen Probiotics SPF55
NDC: 73418-101 | Form: LOTION
Manufacturer: Hello Bello
Category: otc | Type: HUMAN OTC DRUG LABEL
Date: 20250108

ACTIVE INGREDIENTS: ZINC OXIDE 200 mg/1 g
INACTIVE INGREDIENTS: CALENDULA OFFICINALIS FLOWER; TOCOPHEROL; TRIETHYL CITRATE; COCO GLUCOSIDE; HYALURONATE SODIUM; ARACHIDYL ALCOHOL; POLYHYDROXYSTEARIC ACID STEARATE; ARACHIDYL GLUCOSIDE; CAPRYLHYDROXAMIC ACID; CAPRYLOYL GLYCERIN/SEBACIC ACID COPOLYMER (2000 MPA.S); SODIUM GLUCONATE; WATER; CETOSTEARYL ALCOHOL; CAPRYLYL GLYCOL; CARBOXYMETHYLCELLULOSE SODIUM; DOCOSANOL; CETYL ALCOHOL; JOJOBA OIL; SODIUM STEAROYL GLUTAMATE; COCOA BUTTER; VANILLA; BUTYLOCTYL SALICYLATE; CHAMOMILE; GLYCERIN; METHYL DIHYDROABIETATE; OAT KERNEL OIL; CITRIC ACID MONOHYDRATE; ORANGE OIL; COCONUT OIL; DIHEPTYL SUCCINATE; AVOCADO; APRICOT KERNEL OIL; LEVOMENOL; SHEA BUTTER; CUCUMBER; MICROCRYSTALLINE CELLULOSE

Baby Mineral Sunscreen + Probiotics SPF55+

Active Ingredients

Zinc Oxide 20.0%

Purpose

Sunscreen

Uses

- Helps prevent sunburn
- If used as directed with other sun protection measures (see Directions), decreases the risk of skin cancer and early skin aging caused by the sun

Warnings

For external use only

Do not use on

broken or damaged skin

When using this product

Keep out of eyes. Rinse with water to remove

Stop use and ask a doctor if

rash occurs

Keep out of reach of children.

If swallowed, get medical help or contact a Poison Control Center right away

Directions

- Apply liberally and spread evenly by hand 15 minutes before sun exposure
- Reapply: • after 80 minutes of swimming or sweating • immediately after towel use • at least every 2 hours
- For children under 6 months of age, ask a doctor
- Sun Protection Measures: Spending time in the sun can increase your risk of skin cancer and early skin aging. To decrease this risk, regularly use sunscreen with a Broad Spectrum SPF value of 15 or higher and other sun protection measures including: • Limit time in the sun, especially from 10a.m. - 2p.m. • Wear long-sleeved shirts, pants, hats and sunglasses

Other Information

- Protect the product in this container from excessive heat and direct sun
- Avoid long-term exposure storage above 40°C (104°F)
- May stain some fabrics

Inactive Ingredients

Water (Aqua), Cocos Nucifera (Coconut) Oil*, Butyloctyl Salicylate, Diheptyl Succinate, Methyl Dihydroabietate, Butyrospermum Parkii (Shea) Butter*, Capryloyl Glycerin/Sebacic Acid Copolymer, Sodium Stearoyl Glutamate, Cetearyl Alcohol, Microcrystalline Cellulose, Arachidyl Alcohol, Theobroma Cacao (Cocoa) Seed Butter, Tocopherol, Cetyl Alcohol, Caprylyl Glycol, Coco Glucoside, Behenyl Alcohol, Citrus Aurantium Dulcis (Orange) Peel Oil, Polyhydroxystearic Acid, Bisabolol*, Arachidyl Glucoside, Sodium Gluconate, Sodium Hyaluronate, Citric Acid, Triethyl Citrate, Glycerin, Caprylhydroxamic Acid, Cellulose Gum, Vanilla Planifolia Fruit Extract, Prunus Armeniaca (Apricot) Kernel Oil*, Simmondsia Chinensis (Jojoba) Seed Oil*, Chamomilla Recutita (Matricaria) Flower Extract*, Avena Sativa (Oat) Kernel Oil, Bacillus Ferment, Persea Gratissima (Avocado) Fruit Extract*, Calendula Officinalis Flower Extract*, Cucumis Sativus (Cucumber) Fruit Extract*

*Organic

Questions?

(888)860-6888